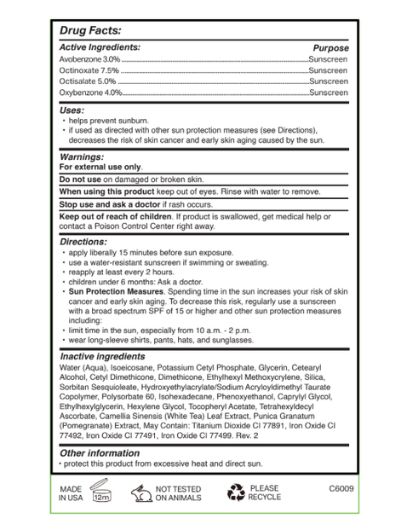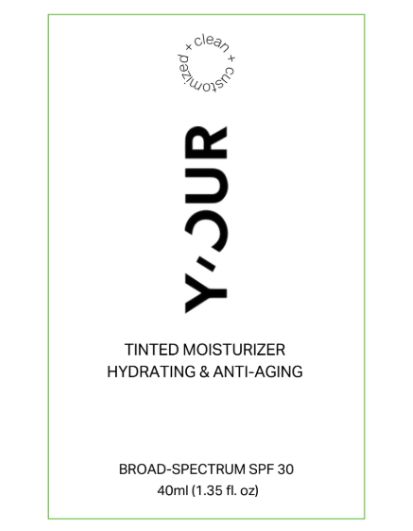 DRUG LABEL: YOUR TINTED MOISTURIZER HYDRATING ANTI AGING BROAD SPECTRUM SPF 30
NDC: 84229-1001 | Form: CREAM
Manufacturer: Skin Ai, LLC
Category: otc | Type: HUMAN OTC DRUG LABEL
Date: 20250201

ACTIVE INGREDIENTS: AVOBENZONE 3 g/100 g; OCTINOXATE 7.5 g/100 g; OCTISALATE 5 g/100 g; OXYBENZONE 4 g/100 g
INACTIVE INGREDIENTS: POTASSIUM CETYL PHOSPHATE; DIMETHICONE; ETHYLHEXYL METHOXYCRYLENE; PUNICA GRANATUM LEAF; ISOHEXADECANE; ETHYLHEXYLGLYCERIN; HEXYLENE GLYCOL; IRON OXIDES; CETYL DIMETHICONE/BIS-VINYLDIMETHICONE CROSSPOLYMER; POLYSORBATE 60; CAMELLIA SINENSIS LEAF; CETEARYL ALCOHOL; SILICA; ISOEICOSANE; TITANIUM DIOXIDE; CAPRYLYL GLYCOL; TETRAHEXYLDECYL ASCORBATE; WATER; GLYCERIN; ALPHA-TOCOPHEROL ACETATE; SORBITAN SESQUIOLEATE; ACRYLAMIDE/SODIUM ACRYLOYLDIMETHYLTAURATE COPOLYMER (120000 MPA.S AT 1%); PHENOXYETHANOL

ACTIVE INGREDIENT

Avobenzone 3.0% - Sunscreen

Octinoxate 7.5% - Sunscreen

Octisalate 5.0% - Sunscreen

Oxybenzone 4.0% - Sunscreen

Uses:

• helps prevent sunburn.
• if used as directed with other sun protection measures (see Directions),
decreases the risk of skin cancer and early skin aging caused by the sun.

Do not use on damaged or broken skin.

When using this product keep out of eyes. Rinse with water to remove.

Stop use and ask a doctor if rash occurs.

Keep out of reach of children. If product is swallowed, get medical help or contact a Poison Control Center right away.

Directions:

• apply liberally 15 minutes before sun exposure.
• use a water-resistant sunscreen if swimming or sweating.
• reapply at least every 2 hours.
• children under 6 months: Ask a doctor.
• Sun Protection Measures. Spending time in the sun increases your risk of skin
cancer and early skin aging. To decrease this risk, regularly use a sunscreen
with a broad spectrum SPF of 15 or higher and other sun protection measures
including:
• limit time in the sun, especially from 10 a.m. - 2 p.m.
• wear long-sleeve shirts, pants, hats, and sunglasses.

Inactive ingredients

Water (Aqua), Isoeicosane, Potassium Cetyl Phosphate, Glycerin, Cetearyl Alcohol, Cetyl Dimethicone, Dimethicone, Ethylhexyl Methoxycrylene, Silica, Sorbitan Sesquioleate, Hydroxyethylacrylate/Sodium Acryloyldimethyl Taurate Copolymer, Polysorbate 60, Isohexadecane, Phenoxyethanol, Caprylyl Glycol, Ethylhexylglycerin, Hexylene Glycol, Tocopheryl Acetate, Tetrahexyldecyl Ascorbate, Camellia Sinensis (White Tea) Leaf Extract, Punica Granatum (Pomegranate) Extract, May Contain: Titanium Dioxide CI 77891, Iron Oxide CI 77492, Iron Oxide CI 77491, Iron Oxide CI 77499. Rev. 2

Other information

• protect this product from excessive heat and direct sun.

PURPOSE

For external use only.

PACKAGE LABEL

TINTED MOISTURIZER
HYDRATING & ANTI-AGING

BROAD-SPECTRUM SPF 30

40ml (1.35 fl. oz)